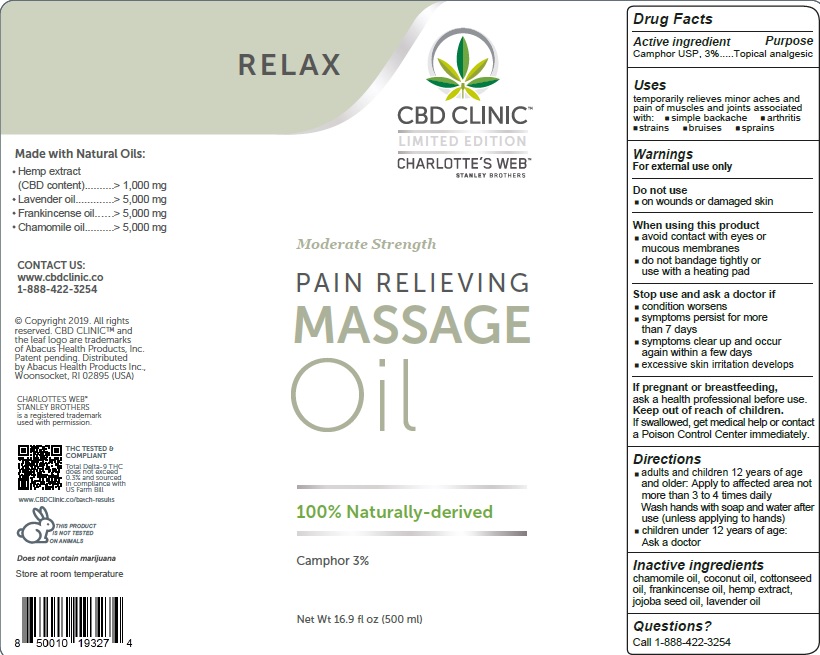 DRUG LABEL: CBD Clinic Relax Massage
NDC: 24909-756 | Form: OIL
Manufacturer: Aidance Skincare & Topical Solutions, LLC
Category: otc | Type: HUMAN OTC DRUG LABEL
Date: 20191229

ACTIVE INGREDIENTS: CAMPHOR (NATURAL) 3 g/100 mL
INACTIVE INGREDIENTS: CHAMOMILE FLOWER OIL; COCONUT OIL; COTTONSEED OIL; FRANKINCENSE OIL; HEMP; JOJOBA OIL; LAVENDER OIL

CBD Clinic Relax Massage

Active Ingredients

Camphor USP, 3%

Purpose

Camphor - Topical Analgesic

Uses

temporarily relieves minor aches and pain of muscles and joints associated with:
• simple backache • arthritis • strains • bruises • sprains

Warnings

For external use only
Do not use on
• wounds or damaged skin
When using this product
• avoid contact with eyes or mucous membranes
• do not bandage tightly or use with a heating pad
Stop use and ask a doctor if
• condition worsens
• symptoms persist for more than 7 days
• symptoms clear up and occur again within a few days
• excessive skin irritation develops
If pregnant or breast-feeding
ask a health professional before use
Keep out of reach of children
If swallowed, get medical help or contact a Poison Control Center immediately

Directions

• adults and children 12 years of age and older:
apply to affected area not more than 3 to 4 times daily.
Wash hands with soap and water after use (unless applying to hands)
• children under 12 years of age: ask a doctor

Inactive Ingredients

chamomile oil, coconut oil, cottonseed oil, frankincense oil, hemp extract, jojoba seed oil, lavender oil

Questions?

Call 1-888-422-3254